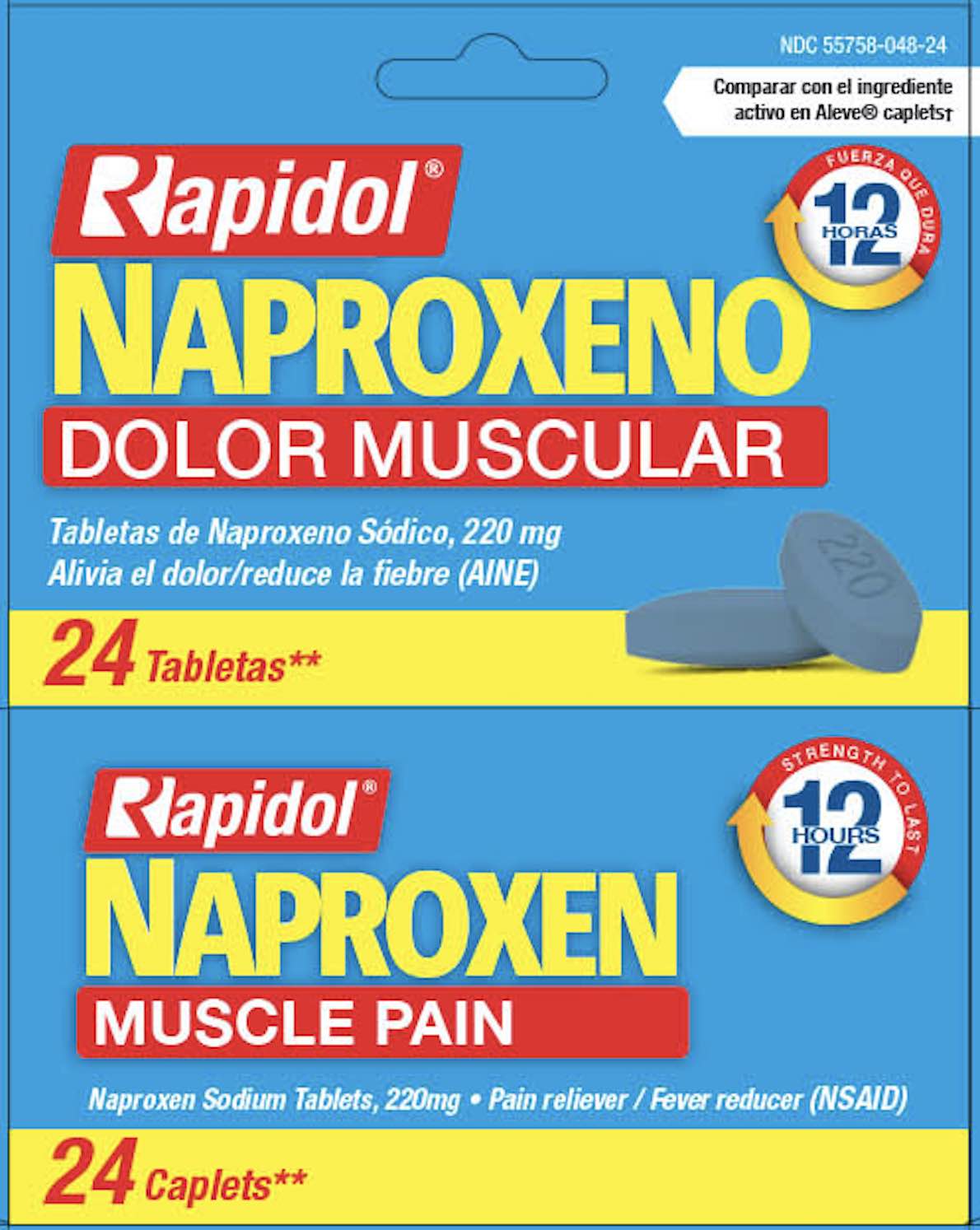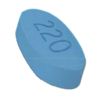 DRUG LABEL: Rapidol Naproxen
NDC: 55758-048 | Form: TABLET, COATED
Manufacturer: Pharmadel LLC
Category: otc | Type: HUMAN OTC DRUG LABEL
Date: 20250204

ACTIVE INGREDIENTS: NAPROXEN SODIUM 220 mg/1 1
INACTIVE INGREDIENTS: HYPROMELLOSE, UNSPECIFIED; FD&C BLUE NO. 2--ALUMINUM LAKE; STARCH, CORN; MICROCRYSTALLINE CELLULOSE; POVIDONE K30; SODIUM STARCH GLYCOLATE TYPE A; TITANIUM DIOXIDE; POLYETHYLENE GLYCOL, UNSPECIFIED; STEARIC ACID; WATER

Rapidol Naproxen 220mg (HHH)

Drug Facts

Active ingredient and Purposes

Active ingredient (in each caplet) | Purposes
Naproxen sodium 220mg; (naproxen 200mg) (NSAID*) | Pain reliver/ fever reducer
*nonsteroidal anti-inflammatory drug

Uses

- temporarily relieves minor aches and pains due to
- minor pain from arthritis
- menstrual cramps
- muscular aches
- headache
- backache
- toothache
- the common cold
- temporarily reduces fever

Warnings

Allergy alert: Naproxen sodium may cause severe skin reactions. Symptoms may include:

- hives
- facial swelling
- asthma (wheezing)
- shock
- skin reddening
- rash
- blisters. If an allergic reaction occurs, stop use and seek medical help right away.

Stomach bleeding warning: This product contains an NSAID, which may cause severe stomach bleeding. The chance is higher if you:

- are age 60 or older
- have had stomach ulcers or bleeding problems
- take a blood thinning (anticoagulant) or steroid drug
- take other drugs containing prescription or nonprescription NSAIDs (aspirin, ibuprofen, naproxen or others)
- have 3 or more alcoholic drinks every day while using this product
- take more or for a longer time than directed

Heart attack and stroke warning:NSAIDs, except aspirin, increase the risk of heart attack, heart failure, and stroke. These can be fatal. The risk is higher if you use more than directed or for longer than directed.

Do not use

- if you have ever had an allergic reaction to any other pain reliever/fever reducer
- right before or after heart surgery

Ask a doctor before use if

- the stomach bleeding warning applies to you
- you have a history of stomach problems, such as heartburn
- you have high blood pressure, heart disease, liver cirrhosis, kidney disease, asthma, or had a stroke
- you are taking a diuretic
- you have problems or serious side effects from taking pain relievers or fever reducers

Ask a doctor or pharmacist before use if you are

- under a doctor’s care for any serious condition
- taking aspirin for heart attack or stroke, because naproxen may decrease this benefit of aspirin
- taking any other drugs

When using this product

- take with food or milk if stomach upset occurs

Stop use and ask a doctor if

- you experience any of the following signs of stomach bleeding:
- feel faint
- vomit blood
- have bloody or black stools
- have stomach pain that does not get better
- you have symptoms of heart problems or stroke:
- chest pain
- trouble breathing
- slurred speech
- leg swelling
- weakness in one part or side of body

- pain gets worse or lasts more than 10 days
- fever gets worse or lasts more than 3 days
- you have difficulty swallowing
- it feels like the pill is stuck in your throat
- redness or swelling is present in the painful area
- any new symptoms appear

If pregnant or breast-feeding,

ask a health professional before use. It is especially important not to use naproxen sodium at 20 weeks or later of pregnancy unless definitely directed to do so by a doctor because it may cause problems in the unborn child or complications during delivery.

KEEP OUT OF REACH OF CHILDREN.

In case of overdose, get medical help or contact a Poison Control Center right away (1-800-222-1222).

Other information

- each caplet contains: sodium 20 mg
- store between 68-77°F (20-25°C). Avoid high humidity and excessive heat above 104°F (40°C)

Directions

- do not take more than directed
- the smallest effective dose should be used
- drink a full glass of water with each dose

adults & children 12 years of age and older | - take 1 tablet every 8 to 12 hours while symptoms last - for the first dose you may take 2 tablets within the first hour - do not exceed 2 tablets in any 8 to 12 hour period - do not exceed 3 Tablets in a 24-hour period
children under 12 years of age | - consult a doctor

Inactive ingredients

corn starch, FD&C blue #2 aluminum lake, hypromellose, microcrystalline cellulose, polyethylene glycol, povidone k30, sodium starch glycolate, stearic acid, titanium dioxide, water

Distributed by/ Distribuido por:

PHARMADEL LLC

New Castle, DE 19720

Questions? +1-866-359-3478

Made in India/ Hecho en India

†This product is not manufactured or distributed by Bayer Health Care LLC., distributor of Aleve® caplets. Aleve® is a registered mark of Bayer Health Care LLC.